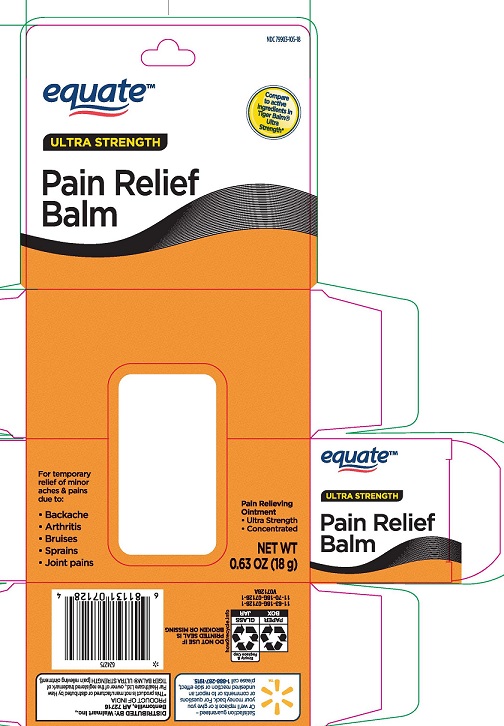 DRUG LABEL: Equate Pain Relief Balm
NDC: 79903-105 | Form: OINTMENT
Manufacturer: WALMART, INC
Category: otc | Type: HUMAN OTC DRUG LABEL
Date: 20251008

ACTIVE INGREDIENTS: MENTHOL 110 mg/1 g; CAMPHOR (SYNTHETIC) 110 mg/1 g
INACTIVE INGREDIENTS: CAJUPUT OIL; CLOVE OIL; CHINESE CINNAMON OIL; PARAFFIN

EQUATE ULTRA STRENGTH PAIN RELIEF BALM – MENTHOL 11% & CAMPHOR 11%

ACTIVE INGREDIENTS

Camphor 11%

Menthol 11%

PURPOSE

Topical analgesic

USES

For temporary relief of minor aches and pains of muscles and joints associated with simple backache, arthritis, bruises, strains and sprains.

WARNINGS

For external use only.

When using this product

- use only as directed.
- avoid contact with eye and mucous membranes
- do not apply to wounds, damaged or irritated skin
- do not bandage or cover with wrap or heating pad
- do not use 1 hour prior to bathing or within 30 minutes after bathing

Stop use an ask a doctor if

- condition worsens
- severe skin irritation occurs
- pain persists for more than 7 days
- pain clears up and then recurs a few days later

If pregnant or breat-feeding, or if you have sensitive skin,

ask a healthcare professional before use.

Keep out of reach of children.

If swallowed, get medical help or contact a Poison Control Center immediately (1-800-222-1222).

DIRECTIONS

- for adults and children over 12 years: rub well on the affected area. Repeat 3 to 4 times daily
- for children 12 years of age or younger: consult a doctor before use

OTHER INFORMATION

This product may cause allergic reaction on some individuals. Test on a small area before use.

INACTIVE INGREDIENTS

cajuput oil, cassia oil, clove oil, dementholized mint oil, paraffin base

QUESTIONS OR COMMENTS

Call 1-888-287-1915